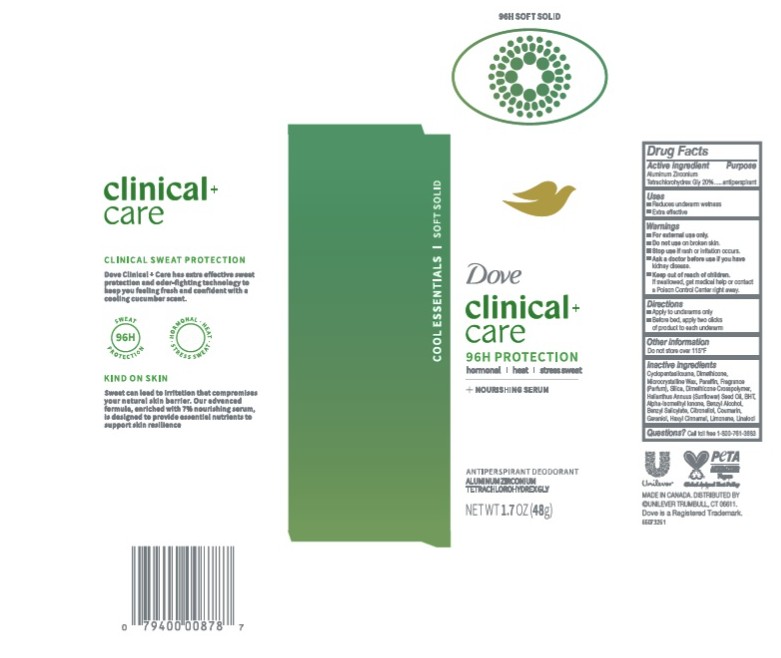 DRUG LABEL: Dove Clinical Care
NDC: 64942-2423 | Form: STICK
Manufacturer: Conopco Inc. d/b/a/ Unilever
Category: otc | Type: HUMAN OTC DRUG LABEL
Date: 20260211

ACTIVE INGREDIENTS: ALUMINUM ZIRCONIUM TETRACHLOROHYDREX GLY 20 g/100 g
INACTIVE INGREDIENTS: SILICA; DIMETHICONE CROSSPOLYMER; CYCLOPENTASILOXANE; HEXYL CINNAMAL; LINALOOL; GERANIOL; BENZYL SALICYLATE; LIMONENE, (+)-; COUMARIN; CITRONELLOL; MICROCRYSTALLINE WAX; PARAFFIN; BENZYL ALCOHOL; DIMETHICONE; BHT; ALPHA-ISOMETHYL IONONE; HELIANTHUS ANNUUS (SUNFLOWER) SEED OIL

Dove Clinical Care Cool Essentials Soft Solid 96H Protection Antiperspirant Deodorant

DESCRIPTION

Dove Clinical + Care Cool Essentials Soft Solid 96H Protection Antiperspirant Deodorant

ACTIVE INGREDIENT

Aluminum Zirconium Tetrachlorohydrex Gly 20%

PURPOSE

Antiperspirant

INDICATIONS AND USAGE

Reduces underarm wetness

Extra effective

WARNINGS

- For external use only.
- Do not use on broken skin.
- Stop use if rash or irritation occurs.
- Ask a doctor before use if you have kidney disease

Keep out of reach of children. If swallowed, get medical help or contact a Poison Control Center right away

DOSAGE AND ADMINISTRATION

apply to underarms only.

Before bed, apply two clicks of product to each underarm

OTHER SAFETY INFORMATION

Do not store over 115°F

INACTIVE INGREDIENT

Cyclopentasiloxane, Dimethicone, Microcrystalline Wax, Paraffin, Fragrance (Parfum), Silica, Dimethicone Crosspolymer, Helianthus Annuus (Sunflower) Seed Oil, BHT, Alpha-Isomethyl Ionone, Benzyl Alcohol, Benzyl Salicylate, Citronellol, Coumarin, Geraniol, Hexyl Cinnamal, Limonene, Linalool

QUESTIONS

call 1-800-761-3683